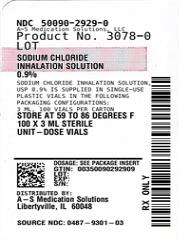 DRUG LABEL: Sodium Chloride
NDC: 50090-2929
Manufacturer: A-S Medication Solutions
Category: other | Type: MEDICAL DEVICE
Date: 20211022

ACTIVE INGREDIENTS: SODIUM CHLORIDE 9 mg/1 mL
INACTIVE INGREDIENTS: Water

Sodium Chloride Inhalation Solution, USP 0.9%